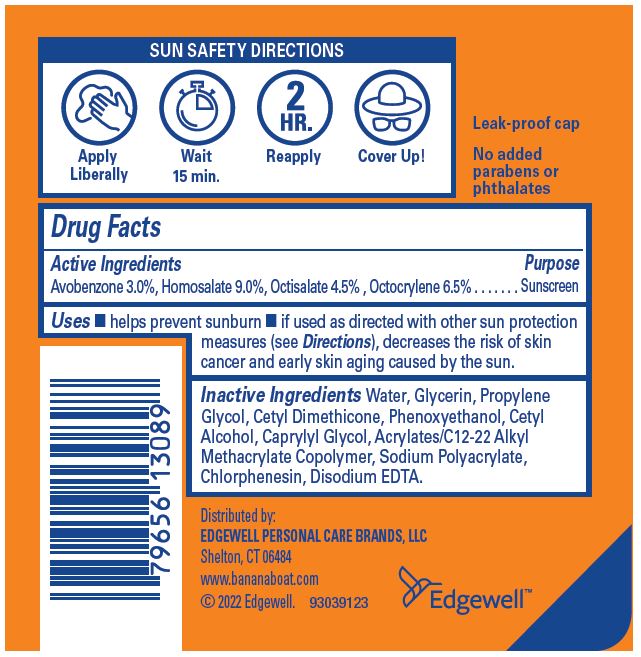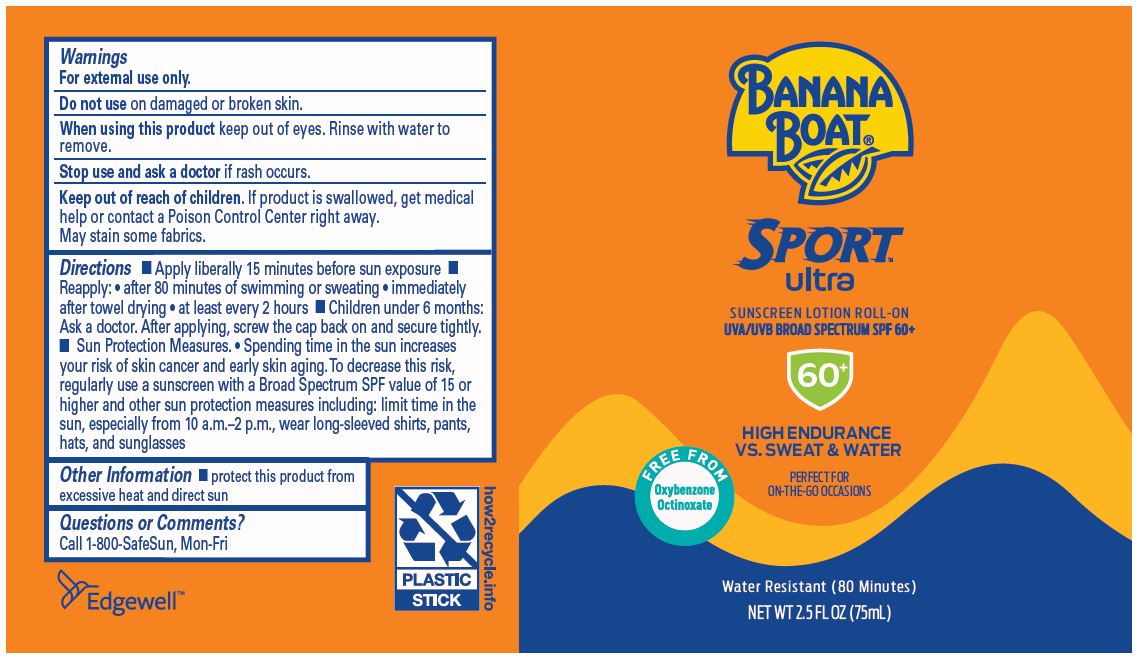 DRUG LABEL: Banana Boat Sport Ultra Sunscreen Roll-On UVA/UVB Broad Spectrum SPF 60 Plus
NDC: 63354-207 | Form: LOTION
Manufacturer: Edgewell Personal Care Brands LLC
Category: otc | Type: HUMAN OTC DRUG LABEL
Date: 20231115

ACTIVE INGREDIENTS: HOMOSALATE 9 g/100 g; OCTOCRYLENE 6.5 g/100 g; OCTISALATE 4.5 g/100 g; AVOBENZONE 3 g/100 g
INACTIVE INGREDIENTS: GLYCERIN; EDETATE DISODIUM ANHYDROUS; PHENOXYETHANOL; CHLORPHENESIN; PROPYLENE GLYCOL; CETYL ALCOHOL; SODIUM POLYACRYLATE (2500000 MW); WATER; CAPRYLYL GLYCOL

Active Ingredients

Avobenzone 3.0%, Homosalate 9.0%, Octisalate 4.5%, Octocrylene 6.5%

Purpose

Sunscreen

Uses

- helps prevent sunburn
- if used as directed with other sun protection measures (see Directions), decreases the risk of skin cancer and early skin aging caused by the sun.

Warnings

For external use only.

May stain some fabrics.

Do not use

on damaged or broken skin.

When using this product

keep out of eyes. Rinse with water to remove.

Stop use and ask a doctor

if rash occurs.

Keep out of reach of children

If product is swallowed, get medical help or contact a Poison Control Center right away.

Directions

- Apply liberally 15 minutes before sun exposure
- Reapply: • after 80 minutes of swimming or sweating • immediately after towel drying • at least every 2 hours
- Children under 6 months: Ask a doctor. After applying, screw the cap back on and secure tightly.

- Sun Protection Measures. • Spending time in the sun increases your risk of skin cancer and early skin aging. To decrease this risk, regularly use a sunscreen with a Broad Spectrum SPF value of 15 or higher and other sun protection measures including: limit time in the sun, especially from 10 a.m.–2 p.m., wear long-sleeved shirts, pants, hats, and sunglasses

Inactive ingredients

Water, Glycerin, Propylene Glycol, Cetyl Dimethicone, Phenoxyethanol, Cetyl Alcohol, Caprylyl Glycol, Acrylates/C12-22 Alkyl Methacrylate Copolymer, Sodium Polyacrylate, Chlorphenesin, Disodium EDTA.

Other information

- protect this product from excessive heat and direct sun

Questions or Comments?

Call 1-800-SafeSun, Mon-Fri

Principal Display Panel

BANANA
BOAT®
KIDS
SPORT
ultra
SUNSCREEN LOTION ROLL-ON
UVA/UVB BROAD SPECTRUM SPF 60+
60+
HIGH ENDURANCE
VS. SWEAT & WATER
PERFECT FOR
ON-THE-GO OCCASIONS
FREE FROM
Oxybenzone
Octinoxate
Water Resistant (80 Minutes)
NET WT 2.5 FL OZ (75mL)